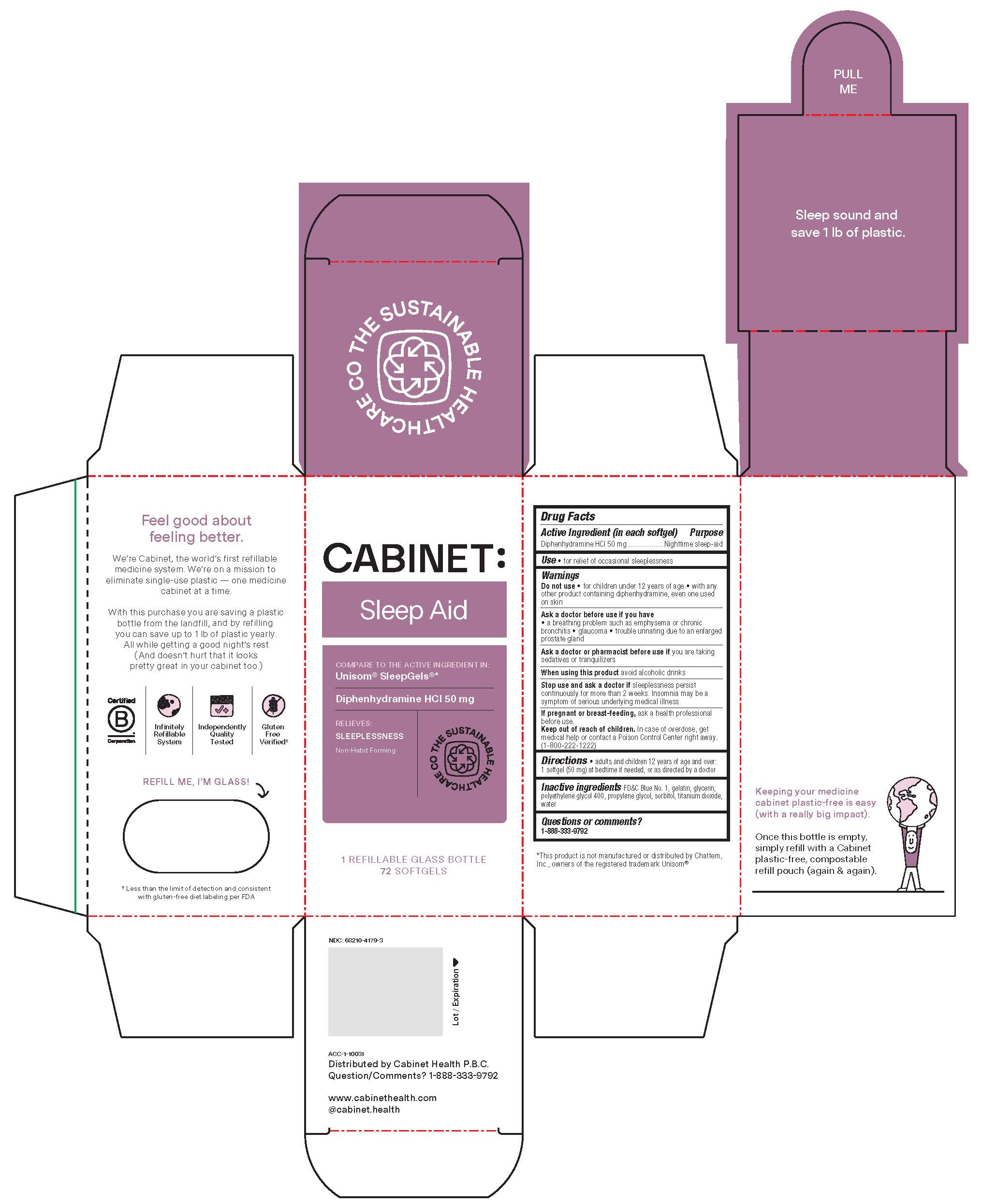 DRUG LABEL: SLEEP AID
NDC: 68210-4227 | Form: CAPSULE, LIQUID FILLED
Manufacturer: SPIRIT PHARMACEUTICALS LLC
Category: otc | Type: HUMAN OTC DRUG LABEL
Date: 20241230

ACTIVE INGREDIENTS: DIPHENHYDRAMINE HYDROCHLORIDE 50 mg/1 1
INACTIVE INGREDIENTS: GELATIN; GLYCERIN; FD&C BLUE NO. 1; POLYETHYLENE GLYCOL 400; PROPYLENE GLYCOL; SORBITOL; TITANIUM DIOXIDE; WATER

SLEEP AID

Drug Facts

Active ingredient (in each softgel)

Diphenhydramine HCL 50 mg

Purpose

Nighttime sleep-aid

Uses

- for relief of occasional sleeplessness

Warnings

Do not use

- for children under 12 years of age
- with any other product containing diphenhydramine, even one used on skin

Ask a doctor before use if you have

- a breathing problem such as emphysema or chronic bronchitis
- glaucoma
- trouble urinating due to an enlarged prostate gland

Ask a doctor or pharmacist before use if you are taking sedatives or tranquilizers

When using this product

avoid alcoholic drinks

Stop use and ask a doctor if

sleeplessness persist continuously for more than 2 weeks. Insomnia may be a symptom of serious underlying medical illness.

PREGNANCY OR BREAST FEEDING

If pregnant or breast-feeding, ask a health professional before use.

keep out of reach of children.

In case of overdose, get medical help or contact a Poison Control Center right away. 1(800)222-1222

Directions

- adults and children 12 years of age and over: 1 softgel (50 mg) at bedtime if needed, or as directed by a doctor

Inactive ingredients

FD&C Blue#1, gelatin, glycerin, polyethylene glycol-400, propylene glycol, sorbitol, titanium dioxide, water

Questions or comments?

1-888-333-9792